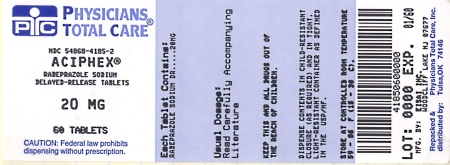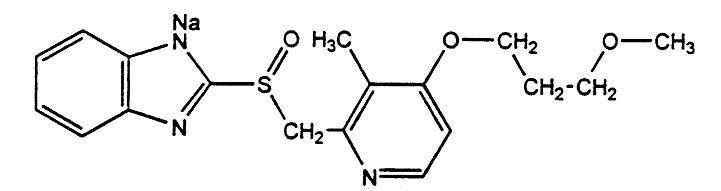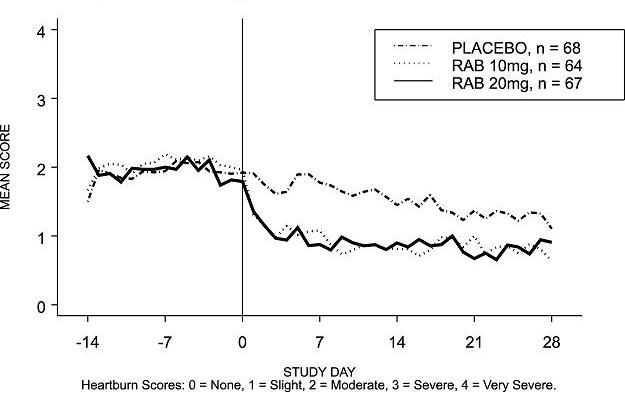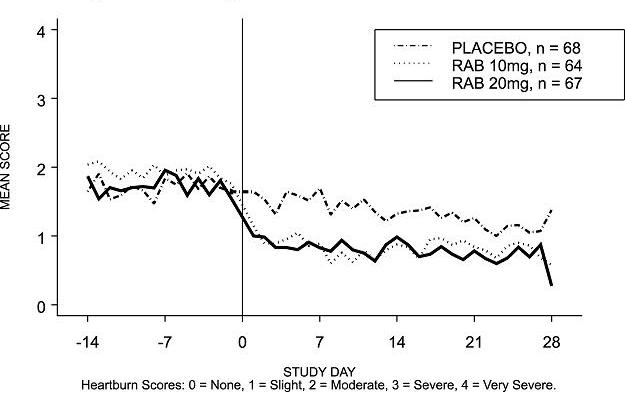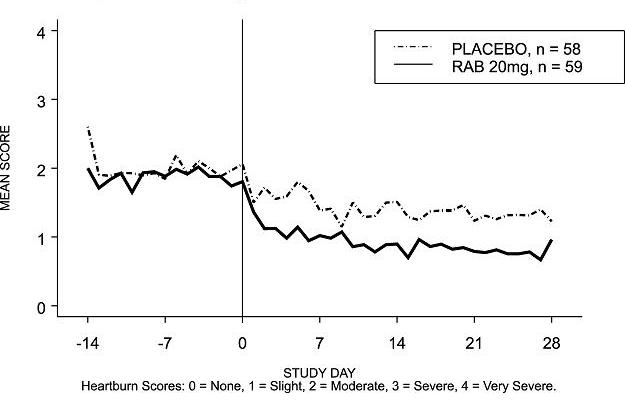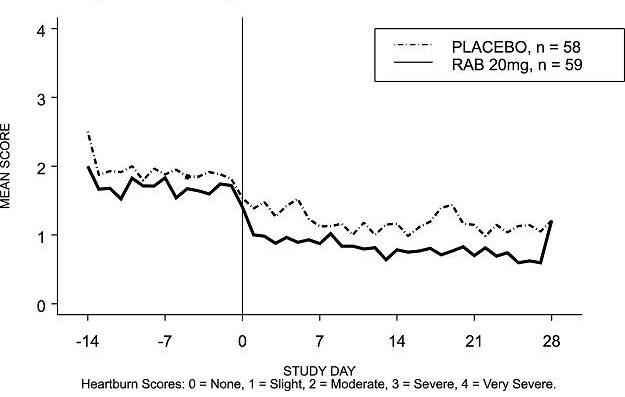 DRUG LABEL: Aciphex
NDC: 54868-4185 | Form: TABLET, DELAYED RELEASE
Manufacturer: Physicians Total Care, Inc.
Category: prescription | Type: HUMAN PRESCRIPTION DRUG LABEL
Date: 20101110

ACTIVE INGREDIENTS: RABEPRAZOLE SODIUM 20 mg/1 1
INACTIVE INGREDIENTS: CARNAUBA WAX; CROSPOVIDONE; ETHYLCELLULOSES; HYDROXYPROPYL CELLULOSE; MAGNESIUM STEARATE; MANNITOL; SODIUM HYDROXIDE; SODIUM STEARYL FUMARATE; TALC; TITANIUM DIOXIDE; FERRIC OXIDE YELLOW

HIGHLIGHTS OF PRESCRIBING INFORMATION

These highlights do not include all the information needed to use ACIPHEX safely and effectively. See full prescribing information for ACIPHEX. ACIPHEX (rabeprazole sodium) tablet, delayed release for oral use Initial U.S. Approval: 1999

RECENT MAJOR CHANGES

Indication and Usage (1.3) June/2008

Dosage and Administration, Pediatric Patients (2.7) June/2008

Use in Specific Populations, Pediatric Use (8.4) June/2008

1 INDICATIONS AND USAGE

ACIPHEX is a proton-pump inhibitor indicated for:

- Healing of Erosive or Ulcerative Gastroesophageal Reflux Disease (GERD) (1.1)
- Maintenance of Healing of Erosive or Ulcerative GERD (1.2)
- Treatment of Symptomatic GERD (1.3)
- Healing of Duodenal Ulcers (1.4)
- Helicobacter pylori Eradication to Reduce the Risk of Duodenal Ulcer Recurrence (1.5)
- Treatment of Pathological Hypersecretory Conditions, Including Zollinger-Ellison Syndrome (1.6)

ACIPHEX is a proton-pump inhibitor indicated for adolescent patients 12 years of age and above for:

- Short-term treatment of Symptomatic GERD (1.3)

2 DOSAGE AND ADMINISTRATION

ACIPHEX tablets should be swallowed whole. The tablets should not be chewed, crushed or split.

Healing of Erosive or Ulcerative Gastroesophageal Reflux Disease (GERD) (2.1)
20 mg once daily

Maintenance of Healing of Erosive or Ulcerative GERD (2.2)
20 mg once daily

Treatment of Symptomatic GERD (2.3)
20 mg once daily

Healing of Duodenal Ulcers (2.4)
20 mg once daily after morning meal

Helicobacter pylori Eradication to Reduce the Risk of Duodenal Ulcer Recurrence (2.5)
Three Drug Regimen All three medications should be taken twice daily with morning and evening meals for 7 days:
ACIPHEX 20 mg
Amoxicillin 1000 mg
Clarithromycin 500 mg

Treatment of Pathological Hypersecretory Conditions, Including Zollinger-Ellison Syndrome (2.6)
Starting dose 60 mg once daily then adjust to patient needs

Short-term Treatment of GERD in Adolescent Patients 12 Years of Age and Above (2.7)
20 mg once daily for up to 8 weeks

3 DOSAGE FORMS AND STRENGTHS

- Tablets: 20 mg (3)

4 CONTRAINDICATIONS

- History of hypersensitivity to rabeprazole (4.1)

5 WARNINGS AND PRECAUTIONS

- Symptomatic response to therapy with rabeprazole does not preclude the presence of gastric malignancy. (5.4)
- Patients treated with a proton pump inhibitor and warfarin may need to be monitored for increases in INR and prothrombin time due to risk of abnormal bleeding. (5.5)

6 ADVERSE REACTIONS

- In the adult studies (4 to 8 weeks), there are no adverse reactions that occur at a rate greater than 5% and greater than placebo (6.1)
- In the adolescent patient studies, adverse reactions were similar to those found in adults (6.1)

To report SUSPECTED ADVERSE REACTIONS, contact Eisai Inc. at 1-888-274-2378 or FDA at 1-800-FDA-1088 or www.fda.gov/medwatch

7 DRUG INTERACTIONS

- Increase INR and prothrombin times have been reported with concomitant use with warfarin. Patients need to be monitored (7.2)
- Rabeprazole has been shown to inhibit cyclosporine metabolism in vitro (7.3)
- ACIPHEX inhibits gastric acid secretion and may interfere with the absorption of drugs where gastric pH is an important determinant of bioavailability (e.g., ketoconazole, iron salts and digoxin) (7.4)
- ACIPHEX may reduce the plasma levels of atazanavir (7.4)

8 USE IN SPECIFIC POPULATIONS

- The safety and efficacy of ACIPHEX for GERD have not been established for pediatric patients less than 12 years of age.
- The safety and efficacy of ACIPHEX for the other adult indications have not been established for pediatric patients.

FULL PRESCRIBING INFORMATION

RECENT MAJOR CHANGES

Enter section text here

1 INDICATIONS AND USAGE

Enter section text here

1.1 Healing of Erosive or Ulcerative GERD

ACIPHEX is indicated for short-term (4 to 8 weeks) treatment in the healing and symptomatic relief of erosive or ulcerative gastroesophageal reflux disease (GERD). For those patients who have not healed after 8 weeks of treatment, an additional 8-week course of ACIPHEX may be considered.

1.2 Maintenance of Healing of Erosive of Ulcerative GERD

ACIPHEX is indicated for maintaining healing and reduction in relapse rates of heartburn symptoms in patients with erosive or ulcerative gastroesophageal reflux disease (GERD Maintenance). Controlled studies do not extend beyond 12 months.

1.3 Treatment of Symptomatic GERD

ACIPHEX is indicated for the treatment of daytime and nighttime heartburn and other symptoms associated with GERD in adults and adolescents 12 years of age and above.

1.4 Healing of Duodenal Ulcers

ACIPHEX is indicated for short-term (up to four weeks) treatment in the healing and symptomatic relief of duodenal ulcers. Most patients heal within four weeks.

1.5 Helicobacter pylori Eradication to Reduce the Risk of Duodenal Ulcer Recurrence

ACIPHEX in combination with amoxicillin and clarithromycin as a three drug regimen, is indicated for the treatment of patients with H. pylori infection and duodenal ulcer disease (active or history within the past 5 years) to eradicate H. pylori. Eradication of H. pylori has been shown to reduce the risk of duodenal ulcer recurrence. {See CLINICAL STUDIES (14.5) and DOSAGE AND ADMINISTRATION (2.5)}

In patients who fail therapy, susceptibility testing should be done. If resistance to clarithromycin is demonstrated or susceptibility testing is not possible, alternative antimicrobial therapy should be instituted. {See CLINICAL PHARMACOLOGY, Microbiology (12.2) and the clarithromycin package insert, CLINICAL PHARMACOLOGY, Microbiology}

1.6 Treatment of Pathological Hypersecretory Conditions, Including Zollinger-Ellison Syndrome

ACIPHEX is indicated for the long-term treatment of pathological hypersecretory conditions, including Zollinger-Ellison syndrome.

2 DOSAGE AND ADMINISTRATION

ACIPHEX tablets should be swallowed whole. The tablets should not be chewed, crushed, or split. ACIPHEX can be taken with or without food.

2.1 Healing of Erosive or Ulcerative GERD

The recommended adult oral dose is one ACIPHEX 20 mg delayed-release tablet to be taken once daily for four to eight weeks {See INDICATIONS AND USAGE.(1.1)}. For those patients who have not healed after 8 weeks of treatment, an additional 8-week course of ACIPHEX may be considered.

2.2 Maintenance of Healing of Erosive or Ulcerative GERD

The recommended adult oral dose is one ACIPHEX 20 mg delayed-release tablet to be taken once daily. {See INDICATIONS AND USAGE (1.2)}.

2.3 Treatment of Symptomatic GERD

The recommended adult oral dose is one ACIPHEX 20 mg delayed-release tablet to be taken once daily for 4 weeks. {See INDICATIONS AND USAGE (1.3)} If symptoms do not resolve completely after 4 weeks, an additional course of treatment may be considered. The recommended adolescent dosing is listed in Section 2.7.

2.4 Healing of Duodenal Ulcers

The recommended adult oral dose is one ACIPHEX 20 mg delayed-release tablet to be taken once daily after the morning meal for a period up to four weeks. {See INDICATIONS AND USAGE (1.4)}. Most patients with duodenal ulcer heal within four weeks. A few patients may require additional therapy to achieve healing.

2.5 Helicobacter pylori Eradication to Reduce the Risk of Duodenal Ulcer Recurrence

TABLE 1 THREE DRUG REGIMENa:
Aciphex | 20 mg | Twice Daily for 7 Days
Amoxicillin | 1000 mg | Twice Daily for 7 Days
Clarithromycin | 500 mg | Twice Daily for 7 Days

All three medications should be taken twice daily with the morning and evening meals.
a It is important that patients comply with the full 7-day regimen. {See CLINICAL STUDIES section.(14.5)}.

2.6 Treatment of Pathological Hypersecretory Conditions Including Zollinger-Ellison Syndrome

The dosage of ACIPHEX in patients with pathologic hypersecretory conditions varies with the individual patient. The recommended adult oral starting dose is 60 mg once a day. Doses should be adjusted to individual patient needs and should continue for as long as clinically indicated. Some patients may require divided doses. Doses up to 100 mg QD and 60 mg BID have been administered. Some patients with Zollinger-Ellison syndrome have been treated continuously with ACIPHEX for up to one year.

2.7 Short-term Treatment of GERD in Adolescent Patients 12 Years of Age and Above

The recommended oral dose for adolescents 12 years of age and above is 20 mg once daily for up to 8 weeks {See Pediatric Use (8.4)}.

2.8 Elderly, Renal and Hepatic Impaired Patients

No dosage adjustment is necessary in elderly patients, in patients with renal disease or in patients with mild to moderate hepatic impairment. Administration of rabeprazole to patients with mild to moderate liver impairment resulted in increased exposure and decreased elimination. Due to the lack of clinical data on rabeprazole in patients with severe hepatic impairment, caution should be exercised in those patients.

3 DOSAGE FORMS AND STRENGTHS

20 mg light yellow enteric-coated delayed release tablets. The name and strength, in mg, (ACIPHEX 20) is imprinted on one side.

4 CONTRAINDICATIONS

Enter section text here

4.1 Hypersensitivity to rabeprazole

Rabeprazole is contraindicated in patients with known hypersensitivity to rabeprazole, substituted benzimidazoles or to any component of the formulation.

4.2 Use of clarithromycin and hypersentivity to macrolide antibiotics

Clarithromycin is contraindicated in patients with known hypersensitivity to any macrolide antibiotic.

4.3 Concomitant use of clarithromycin with pimozide and cisapride

Concomitant administration of clarithromycin with pimozide and cisapride is contraindicated. There have been post-marketing reports of drug interactions when clarithromycin and/or erythromycin are co-administered with pimozide resulting in cardiac arrhythmias (QT prolongation, ventricular tachycardia, ventricular fibrillation, and torsade de pointes) most likely due to inhibition of hepatic metabolism of pimozide by erythromycin and clarithromycin. Fatalities have been reported. (Please refer to full prescribing information for clarithromycin.)

4.4 Amoxicillin and hypersensitivity to penicilllin

Amoxicillin is contraindicated in patients with a known hypersensitivity to any penicillin. (Please refer to full prescribing information for amoxicillin.)

5 WARNINGS AND PRECAUTIONS

Enter section text here

5.1 Clarithromycin use in pregnant women

CLARITHROMYCIN SHOULD NOT BE USED IN PREGNANT WOMEN EXCEPT IN CLINICAL CIRCUMSTANCES WHERE NO ALTERNATIVE THERAPY IS APPROPRIATE. If pregnancy occurs while taking clarithromycin, the patient should be apprised of the potential hazard to the fetus. (See WARNINGS in prescribing information for clarithromycin.)

5.2 Anaphylactic Reactions associated with antibiotic use

Amoxicillin: Serious and occasionally fatal hypersensitivity (anaphylactic) reactions have been reported in patients on penicillin therapy. These reactions are more likely to occur in individuals with a history of penicillin hypersensitivity and/or a history of sensitivity to multiple allergens.

There have been well-documented reports of individuals with a history of penicillin hypersensitivity reactions that have experienced severe hypersensitivity reactions when treated with a cephalosporin. Before initiating therapy with any penicillin, careful inquiry should be made concerning previous hypersensitivity reactions to penicillin, cephalosporin, and other allergens. If an allergic reaction occurs, amoxicillin should be discontinued and the appropriate therapy instituted. (See WARNINGS in prescribing information for amoxicillin.)

SERIOUS ANAPHYLACTIC REACTIONS REQUIRE IMMEDIATE EMERGENCY TREATMENT WITH EPINEPHRINE. OXYGEN, INTRAVENOUS STEROIDS, AND AIRWAY MANAGEMENT, INCLUDING INTUBATION, SHOULD ALSO BE ADMINISTERED AS INDICATED.

5.3 Pseudomembranous colitis associated with antibiotic use

Pseudomembranous colitis has been reported with nearly all antibacterial agents, including clarithromycin and amoxicillin, and may range in severity from mild to life threatening. Therefore, it is important to consider this diagnosis in patients who present with diarrhea subsequent to the administration of antibacterial agents.

Treatment with antibacterial agents alters the normal flora of the colon and may permit overgrowth of clostridia. Studies indicate that a toxin produced by Clostridium difficile is a primary cause of "antibiotic-associated colitis".

After the diagnosis of pseudomembranous colitis has been established, therapeutic measures should be initiated. Mild cases of pseudomembranous colitis usually respond to discontinuation of the drug alone. In moderate to severe cases, consideration should be given to management with fluid and electrolytes, protein supplementation, and treatment with an antibacterial drug clinically effective against Clostridium difficile colitis.

5.4 Presence of Gastric malignancy

Symptomatic response to therapy with rabeprazole does not preclude the presence of gastric malignancy.

Patients with healed GERD were treated for up to 40 months with rabeprazole and monitored with serial gastric biopsies. Patients without H. pylori infection (221 of 326 patients) had no clinically important pathologic changes in the gastric mucosa. Patients with H. pylori infection at baseline (105 of 326 patients) had mild or moderate inflammation in the gastric body or mild inflammation in the gastric antrum. Patients with mild grades of infection or inflammation in the gastric body tended to change to moderate, whereas those graded moderate at baseline tended to remain stable. Patients with mild grades of infection or inflammation in the gastric antrum tended to remain stable. At baseline 8% of patients had atrophy of glands in the gastric body and 15% had atrophy in the gastric antrum. At endpoint, 15% of patients had atrophy of glands in the gastric body and 11% had atrophy in the gastric antrum. Approximately 4% of patients had intestinal metaplasia at some point during follow-up, but no consistent changes were seen.

5.5 Concomitant use with warfarin

Steady state interactions of rabeprazole and warfarin have not been adequately evaluated in patients. There have been reports of increased INR and prothrombin time in patients receiving a proton pump inhibitor and warfarin concomitantly. Increases in INR and prothrombin time may lead to abnormal bleeding and even death. Patients treated with a proton pump inhibitor and warfarin concomitantly may need to be monitored for increases in INR and prothrombin time.

6 ADVERSE REACTIONS

Worldwide, over 2900 patients have been treated with rabeprazole in Phase II-III clinical trials involving various dosages and durations of treatment.

Because clinical trials are conducted under varying conditions, adverse reaction rates observed in the clinical trials of a drug cannot be directly compared to rates in the clinical trials of another drug and may not reflect the rates observed in practice.

6.1 Clinical Studies Experience

The data described below reflect exposure to ACIPHEX in 1064 patients exposed for up to 8 weeks. The studies were primarily placebo- and active-controlled trials in patients with Erosive or Ulcerative Gastroesophageal Reflux Disease (GERD), Duodenal Ulcers and Gastric Ulcers. The population had a mean age of 53 years (range 18-89 years) and had a ratio of approximately 60% male/ 40% female. The racial distribution was 86% Caucasian, 8% African American, 2% Asian and 5% other. Most patients received either 10 mg, 20 mg or 40 mg/day of ACIPHEX.

An analysis of adverse reactions appearing in ≥ 2% of ACIPHEX patients (n= 1064) and with a greater frequency than placebo (n=89) in controlled North American and European acute treatment trials, revealed the following adverse reactions: pain (3% vs. 1%), pharyngitis (3% vs. 2%), flatulence (3% vs. 1%), infection (2% vs. 1%), and constipation (2% vs. 1%). The 3 long-term maintenance studies consisted of a total of 740 patients; at least 54% of patients were exposed to rabeprazole for 6 months while at least 33% were exposed for 12 months. Of the 740 patients, 247 (33%) and 241 (33%) patients received 10 mg and 20 mg of ACIPHEX, respectively, while 169 (23%) patients received placebo and 83 (11%) received omeprazole.

The safety profile of rabeprazole in the maintenance studies was consistent with what was observed in the acute studies

Other adverse events that were seen in controlled clinical trials which do not meet the above criteria (≥2% of ACIPHEX treated patients and > placebo) and for which there is a possibility of a causal relationship to rabeprazole include the following: headache, abdominal pain, diarrhea, dry mouth, dizziness, peripheral edema, hepatic enzyme increase, hepatitis, hepatic encephalopathy, myalgia, and arthralgia.

In a multicenter, open-label study of adolescent patients aged 12 to 16 years with a clinical diagnosis of symptomatic GERD or endoscopically proven GERD, the adverse event profile was similar to that of adults. The adverse reactions reported without regard to relationship to ACIPHEX that occurred in ≥ 2% of 111 patients were headache (9.9%), diarrhea (4.5%), nausea (4.5%), vomiting (3.6%), and abdominal pain (3.6%). The related reported adverse reactions that occurred in ≥ 2% of patients were headache (5.4%) and nausea (1.8%). There were no adverse reactions reported in these studies that were not previously observed in adults.

Combination Treatment with Amoxicillin and Clarithromycin: In clinical trials using combination therapy with rabeprazole plus amoxicillin and clarithromycin (RAC), no adverse reactions unique to this drug combination were observed. In the U.S. multicenter study, the most frequently reported drug related adverse reactions for patients who received RAC therapy for 7 or 10 days were diarrhea (8% and 7%) and taste perversion (6% and 10%), respectively.

No clinically significant laboratory abnormalities particular to the drug combinations were observed.

For more information on adverse reactions or laboratory changes with amoxicillin or clarithromycin, refer to their respective package prescribing information, ADVERSE REACTIONS section.

6.2 Postmarketing Experience

The following adverse reactions have been identified during postapproval use of ACIPHEX. Because these reactions are reported voluntarily from a population of uncertain size, it is not always possible to reliably estimate their frequency or establish a causal relationship to drug exposure: sudden death; coma and hyperammonemia; jaundice; rhabdomyolysis; disorientation and delirium; anaphylaxis; angioedema; bullous and other drug eruptions of the skin; severe dermatologic reactions, including toxic epidermal necrolysis (some fatal), Stevens-Johnson syndrome, and erythema multiforme; interstitial pneumonia; interstitial nephritis; and TSH elevations. In addition, agranulocytosis, hemolytic anemia, leukopenia, pancytopenia, and thrombocytopenia have been reported. Increases in prothrombin time/INR in patients treated with concomitant warfarin have been reported.

7 DRUG INTERACTIONS

Enter section text here

7.1 Drugs metabolized by CYP450

Rabeprazole is metabolized by the cytochrome P450 (CYP450) drug metabolizing enzyme system. Studies in healthy subjects have shown that rabeprazole does not have clinically significant interactions with other drugs metabolized by the CYP450 system, such as warfarin and theophylline given as single oral doses, diazepam as a single intravenous dose, and phenytoin given as a single intravenous dose (with supplemental oral dosing). Steady state interactions of rabeprazole and other drugs metabolized by this enzyme system have not been studied in patients.

7.2 Warfarin

There have been reports of increased INR and prothrombin time in patients receiving proton pump inhibitors, including rabeprazole, and warfarin concomitantly. Increases in INR and prothrombin time may lead to abnormal bleeding and even death.{See WARNINGS AND PRECAUTIONS (5.5)}.

7.3 Cyclosporine

In vitro incubations employing human liver microsomes indicated that rabeprazole inhibited cyclosporine metabolism with an IC50 of 62 micromolar, a concentration that is over 50 times higher than the Cmax in healthy volunteers following 14 days of dosing with 20 mg of rabeprazole. This degree of inhibition is similar to that by omeprazole at equivalent concentrations.

7.4 Compounds dependent on gastric pH for absorption

Rabeprazole produces sustained inhibition of gastric acid secretion. An interaction with compounds which are dependent on gastric pH for absorption may occur due to the magnitude of acid suppression observed with rabeprazole. For example, in normal subjects, co-administration of rabeprazole 20 mg QD resulted in an approximately 30% decrease in the bioavailability of ketoconazole and increases in the AUC and Cmax for digoxin of 19% and 29%, respectively. Therefore, patients may need to be monitored when such drugs are taken concomitantly with rabeprazole. Co-administration of rabeprazole and antacids produced no clinically relevant changes in plasma rabeprazole concentrations.

Concomitant use of atazanavir and proton pump inhibitors is not recommended. Co-administration of atazanavir with proton pump inhibitors is expected to substantially decrease atazanavir plasma concentrations and thereby reduce its therapeutic effect.

7.5 Drugs metabolized by CYP2C19

In a clinical study in Japan evaluating rabeprazole in patients categorized by CYP2C19 genotype (n=6 per genotype category), gastric acid suppression was higher in poor metabolizers as compared to extensive metabolizers. This could be due to higher rabeprazole plasma levels in poor metabolizers. Whether or not interactions of rabeprazole sodium with other drugs metabolized by CYP2C19 would be different between extensive metabolizers and poor metabolizers has not been studied.

7.6 Combined Administration with Clarithromycin

Combined administration consisting of rabeprazole, amoxicillin, and clarithromycin resulted in increases in plasma concentrations of rabeprazole and 14-hydroxyclarithromycin.{See CLINICAL PHARMACOLOGY, Combined Administration with Antimicrobials (12.3)}.

Concomitant administration of clarithromycin with pimozide and cisapride is contraindicated. (See PRECAUTIONS in prescribing information for clarithromycin.) (See PRECAUTIONS in prescribing information for amoxicillin.)

8 USE IN SPECIFIC POPULATIONS

Enter section text here

8.1 Pregnancy

Teratogenic Effects. Pregnancy Category B: Teratology studies have been performed in rats at intravenous doses up to 50 mg/kg/day (plasma AUC of 11.8 μg•hr/mL, about 13 times the human exposure at the recommended dose for GERD) and rabbits at intravenous doses up to 30 mg/kg/day (plasma AUC of 7.3 μg•hr/mL, about 8 times the human exposure at the recommended dose for GERD) and have revealed no evidence of impaired fertility or harm to the fetus due to rabeprazole. There are, however, no adequate and well-controlled studies in pregnant women. Because animal reproduction studies are not always predictive of human response, this drug should be used during pregnancy only if clearly needed.

8.3 Nursing Mothers

Following intravenous administration of ^14C-labeled rabeprazole to lactating rats, radioactivity in milk reached levels that were 2- to 7-fold higher than levels in the blood. It is not known if unmetabolized rabeprazole is excreted in human breast milk. Administration of rabeprazole to rats in late gestation and during lactation at doses of 400 mg/kg/day (about 195-times the human dose based on mg/m^2) resulted in decreases in body weight gain of the pups. Since many drugs are excreted in milk, and because of the potential for adverse reactions to nursing infants from rabeprazole, a decision should be made to discontinue nursing or discontinue the drug, taking into account the importance of the drug to the mother.

8.4 Pediatric Use

Use of ACIPHEX in adolescent patients 12 years of age and above for short-term treatment of GERD is supported by a) extrapolation of results from adequate and well-controlled studies that supported the approval of ACIPHEX for adults {see CLINICAL STUDIES (14.1, 14.2, 14.3) and INDICATIONS AND USAGE (1.1, 1.2, 1.3)};b) safety and pharmacokinetic studies performed in adolescent patients {see Pharmacokinetics, Pediatric (12.3)}. The safety and effectiveness of ACIPHEX for the treatment of GERD patients <12 years of age have not been established. The safety and effectiveness of ACIPHEX for other pediatric indications have not been established.The safety and effectiveness of ACIPHEX for other uses have not been established in pediatric patients.

In a multicenter, randomized, open-label, parallel-group study, 111 adolescents patients 12 to 16 years of age with a clinical diagnosis of symptomatic GERD or suspected or endoscopically proven GERD were randomized and treated with either ACIPHEX 10 mg or ACIPHEX 20 mg once daily for up to 8 weeks for the evaluation of safety and efficacy. The adverse event profile in adolescent patients was similar to that of adults. The related reported adverse events that occurred in >2 % of patients were headache (5.4%) and nausea (1.8%). There were no adverse reactions reported in these studies that were not previously observed in adults.

8.5 Geriatric Use

Of the total number of subjects in clinical studies of ACIPHEX, 19% were 65 years and over, while 4% were 75 years and over. No overall differences in safety or effectiveness were observed between these subjects and younger subjects, and other reported clinical experience has not identified differences in responses between the elderly and younger patients, but greater sensitivity of some older individuals cannot be ruled out.

8.6 Gender

Duodenal ulcer and erosive esophagitis healing rates in women are similar to those in men. Adverse reactions and laboratory test abnormalities in women occurred at rates similar to those in men.

10 OVERDOSAGE

Because strategies for the management of overdose are continually evolving, it is advisable to contact a Poison Control Center to determine the latest recommendations for the management of an overdose of any drug. There has been no experience with large overdoses with rabeprazole. Seven reports of accidental overdosage with rabeprazole have been received. The maximum reported overdose was 80 mg. There were no clinical signs or symptoms associated with any reported overdose. Patients with Zollinger-Ellison syndrome have been treated with up to 120 mg rabeprazole QD. No specific antidote for rabeprazole is known. Rabeprazole is extensively protein bound and is not readily dialyzable. In the event of overdosage, treatment should be symptomatic and supportive.

Single oral doses of rabeprazole at 786 mg/kg and 1024 mg/kg were lethal to mice and rats, respectively. The single oral dose of 2000 mg/kg was not lethal to dogs. The major symptoms of acute toxicity were hypoactivity, labored respiration, lateral or prone position and convulsion in mice and rats and watery diarrhea, tremor, convulsion and coma in dogs.

11 DESCRIPTION

The active ingredient in ACIPHEX Delayed-Release Tablets is rabeprazole sodium, a substituted benzimidazole that inhibits gastric acid secretion. Rabeprazole sodium is known chemically as 2-[[[4-(3-methoxypropoxy)-3-methyl-2-pyridinyl]-methyl]sulfinyl]-1H-benzimidazole sodium salt. It has an empirical formula of C18H20N3NaO3S and a molecular weight of 381.43. Rabeprazole sodium is a white to slightly yellowish-white solid. It is very soluble in water and methanol, freely soluble in ethanol, chloroform and ethyl acetate and insoluble in ether and n-hexane. The stability of rabeprazole sodium is a function of pH; it is rapidly degraded in acid media, and is more stable under alkaline conditions. The structural formula is:

ACIPHEX is available for oral administration as delayed-release, enteric-coated tablets containing 20 mg of rabeprazole sodium.

Inactive ingredients of the 20 mg tablet are carnauba wax, crospovidone, diacetylated monoglycerides, ethylcellulose, hydroxypropyl cellulose, hypromellose phthalate, magnesium stearate, mannitol, propylene glycol, sodium hydroxide, sodium stearyl fumarate, talc, and titanium dioxide. Iron oxide yellow is the coloring agent for the tablet coating. Iron oxide red is the ink pigment.

12 CLINICAL PHARMACOLOGY

Enter section text here

12.1 Mechanism of Action

Rabeprazole belongs to a class of antisecretory compounds (substituted benzimidazole proton-pump inhibitors) that do not exhibit anticholinergic or histamine H2-receptor antagonist properties, but suppress gastric acid secretion by inhibiting the gastric H^+, K^+ATPase at the secretory surface of the gastric parietal cell. Because this enzyme is regarded as the acid (proton) pump within the parietal cell, rabeprazole has been characterized as a gastric proton-pump inhibitor. Rabeprazole blocks the final step of gastric acid secretion.

In gastric parietal cells, rabeprazole is protonated, accumulates, and is transformed to an active sulfenamide. When studied in vitro, rabeprazole is chemically activated at pH 1.2 with a half-life of 78 seconds. It inhibits acid transport in porcine gastric vesicles with a half-life of 90 seconds.

12.2 Pharmacodynamics

Antisecretory Activity

The anti-secretory effect begins within one hour after oral administration of 20 mg ACIPHEX. The median inhibitory effect of ACIPHEX on 24 hour gastric acidity is 88% of maximal after the first dose. ACIPHEX 20 mg inhibits basal and peptone meal-stimulated acid secretion versus placebo by 86% and 95%, respectively, and increases the percent of a 24-hour period that the gastric pH>3 from 10% to 65% (see table below). This relatively prolonged pharmacodynamic action compared to the short pharmacokinetic half-life (1-2 hours) reflects the sustained inactivation of the H^+, K^+ATPase.

TABLE 2 GASTRIC ACID PARAMETERS ACIPHEX VERSUS PLACEBO AFTER 7 DAYS OF ONCE DAILY DOSING
Parameter | ACIPHEX (20 mg QD) | Placebo
Basal Acid Output (mmol/hr) | 0.4* | 2.8
Stimulated Acid Output (mmol/hr) | 0.6* | 13.3
% Time Gastric pH>3 | 65* | 10

*(p<0.01 versus placebo)

Compared to placebo, ACIPHEX, 10 mg, 20 mg, and 40 mg, administered once daily for 7 days significantly decreased intragastric acidity with all doses for each of four meal-related intervals and the 24-hour time period overall. In this study, there were no statistically significant differences between doses; however, there was a significant dose-related decrease in intragastric acidity. The ability of rabeprazole to cause a dose-related decrease in mean intragastric acidity is illustrated below.

TABLE 3 AUC ACIDITY (MMOL•HR/L) ACIPHEX VERSUS PLACEBO ON DAY 7 OF ONCE DAILY DOSING (MEAN±SD)
 | Treatment
AUC interval (hrs) | 10 mg RBP (N=24) | 20 mg RBP (N=24) | 40 mg RBP (N=24) | Placebo (N=24)
08:00 - 13:00 | 19.6±21.5* | 12.9±23* | 7.6±14.7* | 91.1±39.7
13:00 - 19:00 | 5.6±9.7* | 8.3±29.8* | 1.3±5.2* | 95.5±48.7
19:00 - 22:00 | 0.1±0.1* | 0.1±0.06* | 0.0±0.02* | 11.9±12.5
22:00 - 08:00 | 129.2±84* | 109.6±67.2* | 76.9±58.4* | 479.9±165
AUC 0-24 hours | 155.5±90.6* | 130.9±81* | 85.8±64.3* | 678.5±216

*(p<0.001 versus placebo)

After administration of 20 mg ACIPHEX once daily for eight days, the mean percent of time that gastric pH>3 or gastric pH>4 after a single dose (Day 1) and multiple doses (Day 8) was significantly greater than placebo (see table below). The decrease in gastric acidity and the increase in gastric pH observed with 20 mg ACIPHEX administered once daily for eight days were compared to the same parameters for placebo, as illustrated below:

TABLE 4 GASTRIC ACID PARAMETERS ACIPHEX ONCE DAILY DOSING VERSUS PLACEBO ON DAY 1 AND DAY 8
 | ACIPHEX 20 mg QD |  | Placebo
Parameter | Day 1 | Day 8 | Day 1 | Day 8
Mean AUC0-24 Acidity | 340.8* | 176.9* | 925.5 | 862.4
Median trough pH (23-hr)a | 3.77 | 3.51 | 1.27 | 1.38
% Time Gastric pH>3b | 54.6* | 68.7* | 19.1 | 21.7
% Time Gastric pH>4b | 44.1* | 60.3* | 7.6 | 11.0

a No inferential statistics conducted for this parameter.
* (p<0.001 versus placebo)
b Gastric pH was measured every hour over a 24-hour period.

Effects on Esophageal Acid Exposure

In patients with gastroesophageal reflux disease (GERD) and moderate to severe esophageal acid exposure, ACIPHEX 20 mg and 40 mg per day decreased 24-hour esophageal acid exposure. After seven days of treatment, the percentage of time that esophageal pH<4 decreased from baselines of 24.7% for 20 mg and 23.7% for 40 mg, to 5.1% and 2.0%, respectively. Normalization of 24-hour intraesophageal acid exposure was correlated to gastric pH>4 for at least 35% of the 24-hour period; this level was achieved in 90% of subjects receiving ACIPHEX 20 mg and in 100% of subjects receiving ACIPHEX 40 mg. With ACIPHEX 20 mg and 40 mg per day, significant effects on gastric and esophageal pH were noted after one day of treatment, and more pronounced after seven days of treatment.

Effects on Serum Gastrin

In patients given daily doses of ACIPHEX for up to eight weeks to treat ulcerative or erosive esophagitis and in patients treated for up to 52 weeks to prevent recurrence of disease the median fasting gastrin level increased in a dose-related manner. The group median values stayed within the normal range.

In a group of subjects treated daily with ACIPHEX 20 mg for 4 weeks a doubling of mean serum gastrin concentrations were observed. Approximately 35% of these treated subjects developed serum gastrin concentrations above the upper limit of normal. In a study of CYP2C19 genotyped subjects in Japan, poor metabolizers developed statistically significantly higher serum gastrin concentrations than extensive metabolizers.

Effects on Enterochromaffin-like (ECL) Cells

Increased serum gastrin secondary to antisecretory agents stimulates proliferation of gastric ECL cells which, over time, may result in ECL cell hyperplasia in rats and mice and gastric carcinoids in rats, especially in females (see Carcinogenesis, Mutagenesis, Impairment of Fertility (13.1)}.

In over 400 patients treated with ACIPHEX (10 or 20 mg/day) for up to one year, the incidence of ECL cell hyperplasia increased with time and dose, which is consistent with the pharmacological action of the proton-pump inhibitor. No patient developed the adenomatoid, dysplastic or neoplastic changes of ECL cells in the gastric mucosa. No patient developed the carcinoid tumors observed in rats.

Endocrine Effects

Studies in humans for up to one year have not revealed clinically significant effects on the endocrine system. In healthy male volunteers treated with ACIPHEX for 13 days, no clinically relevant changes have been detected in the following endocrine parameters examined: 17 β-estradiol, thyroid stimulating hormone, tri-iodothyronine, thyroxine, thyroxine-binding protein, parathyroid hormone, insulin, glucagon, renin, aldosterone, follicle-stimulating hormone, luteotrophic hormone, prolactin, somatotrophic hormone, dehydroepiandrosterone, cortisol-binding globulin, and urinary 6β-hydroxycortisol, serum testosterone and circadian cortisol profile.

Other Effects

In humans treated with ACIPHEX for up to one year, no systemic effects have been observed on the central nervous, lymphoid, hematopoietic, renal, hepatic, cardiovascular, or respiratory systems. No data are available on long-term treatment with ACIPHEX and ocular effects.

Microbiology

The following in vitro data are available but the clinical significance is unknown.

Rabeprazole sodium, amoxicillin and clarithromycin as a three drug regimen has been shown to be active against most strains of Helicobacter pylori in vitro and in clinical infections as described in the CLINICAL STUDIES (14) and INDICATIONS AND USAGE (1)sections.

Helicobacter pylori

Susceptibility testing of H. pylori isolates was performed for amoxicillin and clarithromycin using agar dilution methodology^1, and minimum inhibitory concentrations (MICs) were determined. The clarithromycin and amoxicillin MIC values should be interpreted according to the following criteria:

TABLE 5 INTERPRETATION OF CLARITHROMYCIN AND AMOXICILLIN MIC VALUES
Clarithromycin MIC (μg/mL) a | Interpretation
≤0.25 0.5 ≥1.0 | Susceptible (S) Intermediate (I) Resistant (R)
Amoxicillin MIC (μg/mL) a,b | Interpretation
≤0.25 | Susceptible (S)

a These are breakpoints for the agar dilution methodology and they should not be used to interpret results using alternative methods.
b There were not enough organisms with MICs > 0.25 μg/mL to determine a resistance breakpoint.

Standardized susceptibility test procedures require the use of laboratory control microorganisms to control the technical aspects of the laboratory procedures. Standard clarithromycin and amoxicillin powders should provide the following MIC values:

TABLE 6 MIC VALUES FOR STANDARD CLARITHROMYCIN AND AMOXICILLIN POWDERS
Microorganism | Antimicrobial Agent | MIC (μg/mL)a
H. pylori ATCC 43504 | Clarithromycin | 0.015 - 0.12 μg/mL
H. pylori ATCC 43504 | Amoxicillin | 0.015 - 0.12 μg/mL

a These are quality control ranges for the agar dilution methodology and they should not be used to control test results obtained using alternative methods.

Incidence of Antibiotic-Resistant Organisms Among Clinical Isolates

Pretreatment Resistance: Clarithromycin pretreatment resistance rate (MIC > 1 μg/mL) to H. pylori was 9% (51/ 560) at baseline in all treatment groups combined. A total of > 99% (558/560) of patients had H. pylori isolates which were considered to be susceptible (MIC < 0.25 μg/mL) to amoxicillin at baseline. Two patients had baseline H. pylori isolates with an amoxicillin MIC of 0.5 μg/mL.

Clarithromycin Susceptibility Test Results and Clinical/Bacteriologic Outcomes: For the U.S. multicenter study, the baseline H. pylori clarithromycin susceptibility results and the H. pylori eradication results post-treatment are shown in the table below:

TABLE 7 CLARITHROMYCIN SUSCEPTIBILITY TEST RESULTS AND CLINICAL/BACTERIOLOGIC OUTCOMES A FOR A THREE DRUG REGIMEN (RABEPRAZOLE 20 MG TWICE DAILY, AMOXICILLIN 1000 MG TWICE DAILY, AND CLARITHROMYCIN 500 MG TWICE DAILY FOR 7 OR 10 DAYS)
Days of RAC Therapy | Clarithromycin Pretreatment Results | Total Number | H. pylori Negative (Eradicated) | H. pylori Positive (Persistent) Post-Treatment Susceptibility Results
Sb | Ib | Rb | No MIC
7 | Susceptible b | 129 | 103 | 2 | 0 | 1 | 23
7 | Intermediate b | 0 | 0 | 0 | 0 | 0 | 0
7 | Resistant b | 16 | 5 | 2 | 1 | 4 | 4
10 | Susceptible b | 133 | 111 | 3 | 1 | 2 | 16
10 | Intermediate b | 0 | 0 | 0 | 0 | 0 | 0
10 | Resistant b | 9 | 1 | 0 | 0 | 5 | 3

a Includes only patients with pretreatment and post-treatment clarithromycin susceptibility test results.
b Susceptible (S) MIC < 0.25 μg/mL, Intermediate (I) MIC = 0.5 μg/mL, Resistant (R) MIC > 1 μg/mL

Patients with persistent H. pylori infection following rabeprazole, amoxicillin, and clarithromycin therapy will likely have clarithromycin resistant clinical isolates. Therefore, clarithromycin susceptibility testing should be done when possible. If resistance to clarithromycin is demonstrated or susceptibility testing is not possible, alternative antimicrobial therapy should be instituted.

Amoxicillin Susceptibility Test Results and Clinical/Bacteriological Outcomes: In the U.S. multicenter study, a total of >99% (558/560) of patients had H. pylori isolates which were considered to be susceptible (MIC < 0.25 μg/mL) to amoxicillin at baseline. The other 2 patients had baseline H. pylori isolates with an amoxicillin MIC of 0.5 μg/mL, and both isolates were clarithromycin-resistant at baseline; in one case the H. pylori was eradicated. In the 7- and 10-day treatment groups 75% (107/145) and 79% (112/142), respectively, of the patients who had pretreatment amoxicillin susceptible MICs (<0.25 μg/mL) were eradicated of H. pylori. No patients developed amoxicillin-resistant H. pylori during therapy.

12.3 Pharmacokinetics

ACIPHEX delayed-release tablets are enteric-coated to allow rabeprazole sodium, which is acid labile, to pass through the stomach relatively intact. After oral administration of 20 mg ACIPHEX, peak plasma concentrations (Cmax) of rabeprazole occur over a range of 2.0 to 5.0 hours (Tmax). The rabeprazole Cmax and AUC are linear over an oral dose range of 10 mg to 40 mg. There is no appreciable accumulation when doses of 10 mg to 40 mg are administered every 24 hours; the pharmacokinetics of rabeprazole are not altered by multiple dosing. The plasma half-life ranges from 1 to 2 hours.

Absorption: Absolute bioavailability for a 20 mg oral tablet of rabeprazole (compared to intravenous administration) is approximately 52%. When rabeprazole is administered with a high fat meal, its Tmax is variable and may delay its absorption up to 4 hours or longer, however, the Cmax and the extent of rabeprazole absorption (AUC) are not significantly altered. Thus rabeprazole may be taken without regard to timing of meals.

Distribution: Rabeprazole is 96.3% bound to human plasma proteins.

Metabolism: Rabeprazole is extensively metabolized. A significant portion of rabeprazole is metabolized via systemic nonenzymatic reduction to a thioether compound. Rabeprazole is also metabolized to sulphone and desmethyl compounds via cytochrome P450 in the liver. The thioether and sulphone are the primary metabolites measured in human plasma. These metabolites were not observed to have significant antisecretory activity. In vitro studies have demonstrated that rabeprazole is metabolized in the liver primarily by cytochromes P450 3A (CYP3A) to a sulphone metabolite and cytochrome P450 2C19 (CYP2C19) to desmethyl rabeprazole. CYP2C19 exhibits a known genetic polymorphism due to its deficiency in some sub-populations (e.g. 3 to 5% of Caucasians and 17 to 20% of Asians). Rabeprazole metabolism is slow in these sub-populations, therefore, they are referred to as poor metabolizers of the drug.

Elimination: Following a single 20 mg oral dose of ^14C-labeled rabeprazole, approximately 90% of the drug was eliminated in the urine, primarily as thioether carboxylic acid; its glucuronide, and mercapturic acid metabolites. The remainder of the dose was recovered in the feces. Total recovery of radioactivity was 99.8%. No unchanged rabeprazole was recovered in the urine or feces.

Geriatric: In 20 healthy elderly subjects administered 20 mg rabeprazole once daily for seven days, AUC values approximately doubled and the Cmax increased by 60% compared to values in a parallel younger control group. There was no evidence of drug accumulation after once daily administration. {see USE IN SPECIAL POPULATIONS Geriatric Use (8.5)}.

Pediatric: The pharmacokinetics of rabeprazole was studied in 12 adolescent patients with GERD 12 to 16 years of age, in a multicenter study. Patients received rabeprazole 20 mg once daily for five or seven days. An approximate 40% increase in exposure was noted following 5 to 7 days of dosing compared with the exposure after 1 day dosing. Pharmacokinetic parameters in adolescent patients with GERD 12 to 16 years of age were within the range observed in healthy adult volunteers.

Gender and Race: In analyses adjusted for body mass and height, rabeprazole pharmacokinetics showed no clinically significant differences between male and female subjects. In studies that used different formulations of rabeprazole, AUC0-∞ values for healthy Japanese men were approximately 50-60% greater than values derived from pooled data from healthy men in the United States.

Renal Disease: In 10 patients with stable end-stage renal disease requiring maintenance hemodialysis (creatinine clearance ≤5 mL/min/1.73 m^2), no clinically significant differences were observed in the pharmacokinetics of rabeprazole after a single 20 mg oral dose when compared to 10 healthy volunteers. (see DOSAGE AND ADMINISTRATION (2.7)}

Hepatic Disease: In a single dose study of 10 patients with chronic mild to moderate compensated cirrhosis of the liver who were administered a 20 mg dose of rabeprazole, AUC0-24 was approximately doubled, the elimination half-life was 2- to 3-fold higher, and total body clearance was decreased to less than half compared to values in healthy men.

In a multiple dose study of 12 patients with mild to moderate hepatic impairment administered 20 mg rabeprazole once daily for eight days, AUC0-∞ and Cmax values increased approximately 20% compared to values in healthy age- and gender-matched subjects. These increases were not statistically significant.

No information exists on rabeprazole disposition in patients with severe hepatic impairment. Please refer to the DOSAGE AND ADMINISTRATION section (2.7) for information on dosage adjustment in patients with hepatic impairment.

Combined Administration with Antimicrobials: Sixteen healthy volunteers genotyped as extensive metabolizers with respect to CYP2C19 were given 20 mg rabeprazole sodium, 1000 mg amoxicillin, 500 mg clarithromycin, or all 3 drugs in a four-way crossover study. Each of the four regimens was administered twice daily for 6 days. The AUC and Cmax for clarithromycin and amoxicillin were not different following combined administration compared to values following single administration. However, the rabeprazole AUC and Cmax increased by 11% and 34%, respectively, following combined administration. The AUC and Cmax for 14-hydroxyclarithromycin (active metabolite of clarithromycin) also increased by 42% and 46%, respectively. This increase in exposure to rabeprazole and 14-hydroxyclarithromycin is not expected to produce safety concerns.

13 NONCLINICAL PHARMACOLOGY

Enter section text here

13.1 Carcinogenesis, Mutagenesis, Impairment of Fertility

In a 88/104-week carcinogenicity study in CD-1 mice, rabeprazole at oral doses up to 100 mg/kg/day did not produce any increased tumor occurrence. The highest tested dose produced a systemic exposure to rabeprazole (AUC) of 1.40 μg•hr/mL which is 1.6 times the human exposure (plasma AUC0-∞ = 0.88 μg•hr/mL) at the recommended dose for GERD (20 mg/day). In a 28-week carcinogenicity study, rabeprazole at oral doses up to 200 mg/kg was orally given to male and female p53+/- transgenic mice (approximately 17-24x human exposure at MRD based on AUC) did not cause an increase in the incidence rates of tumors, while gastric mucosal thickening and hyperplasia, secondary to the pharmacological action, were observed. In a 104-week carcinogenicity study in Sprague-Dawley rats, males were treated with oral doses of 5, 15, 30 and 60 mg/kg/day and females with 5, 15, 30, 60 and 120 mg/kg/day. Rabeprazole produced gastric enterochromaffin-like (ECL) cell hyperplasia in male and female rats and ECL cell carcinoid tumors in female rats at all doses including the lowest tested dose. The lowest dose (5 mg/kg/day) produced a systemic exposure to rabeprazole (AUC) of about 0.1 μg•hr/mL which is about 0.1 times the human exposure at the recommended dose for GERD. In male rats, no treatment related tumors were observed at doses up to 60 mg/kg/day producing a rabeprazole plasma exposure (AUC) of about 0.2 μg•hr/mL (0.2 times the human exposure at the recommended dose for GERD).

Rabeprazole was positive in the Ames test, the Chinese hamster ovary cell (CHO/HGPRT) forward gene mutation test and the mouse lymphoma cell (L5178Y/TK+/-) forward gene mutation test. Its demethylated-metabolite was also positive in the Ames test. Rabeprazole was negative in the in vitro Chinese hamster lung cell chromosome aberration test, the in vivo mouse micronucleus test, and the in vivo and ex vivo rat hepatocyte unscheduled DNA synthesis (UDS) tests.

Rabeprazole at intravenous doses up to 30 mg/kg/day (plasma AUC of 8.8 μg•hr/mL, about 10 times the human exposure at the recommended dose for GERD) was found to have no effect on fertility and reproductive performance of male and female rats.

14 CLINICAL STUDIES

Enter section text here

14.1 Healing of Erosive or Ulcerative GERD

In a U.S., multicenter, randomized, double-blind, placebo-controlled study, 103 patients were treated for up to eight weeks with placebo, 10 mg, 20 mg or 40 mg ACIPHEX QD. For this and all studies of GERD healing, only patients with GERD symptoms and at least grade 2 esophagitis (modified Hetzel-Dent grading scale) were eligible for entry. Endoscopic healing was defined as grade 0 or 1. Each rabeprazole dose was significantly superior to placebo in producing endoscopic healing after four and eight weeks of treatment. The percentage of patients demonstrating endoscopic healing was as follows:

TABLE 8 HEALING OF EROSIVE OR ULCERATIVE GASTROESOPHAGEAL REFLUX DISEASE (GERD) PERCENTAGE OF PATIENTS HEALED
Week | 10 mg ACIPHEX QD N=27 | 20 mg ACIPHEX QD N=25 | 40 mg ACIPHEX QD N=26 | Placebo N=25
4 | 63%* | 56%* | 54%* | 0%
8 | 93%* | 84%* | 85%* | 12%

*(p<0.001 versus placebo)

In addition, there was a statistically significant difference in favor of the ACIPHEX 10 mg, 20 mg, and 40 mg doses compared to placebo at Weeks 4 and 8 regarding complete resolution of GERD heartburn frequency (p<0.026). All ACIPHEX groups reported significantly greater rates of complete resolution of GERD daytime heartburn severity compared to placebo at Weeks 4 and 8 (p<0.036). Mean reductions from baseline in daily antacid dose were statistically significant for all ACIPHEX groups when compared to placebo at both Weeks 4 and 8 (p<0.007).

In a North American multicenter, randomized, double-blind, active-controlled study of 336 patients, ACIPHEX was statistically superior to ranitidine with respect to the percentage of patients healed at endoscopy after four and eight weeks of treatment (see table below):

TABLE 9 HEALING OF EROSIVE OR ULCERATIVE GASTROESOPHAGEAL REFLUX DISEASE (GERD) PERCENTAGE OF PATIENTS HEALED
Week | ACIPHEX 20 mg QD N=167 | Ranitidine 150 mg QID N=169
4 | 59%* | 36%
8 | 87%* | 66%

*(p<0.001 versus ranitidine)

ACIPHEX 20 mg once daily was significantly more effective than ranitidine 150 mg QID in the percentage of patients with complete resolution of heartburn at Weeks 4 and 8 (p<0.001). ACIPHEX 20 mg once daily was also more effective in complete resolution of daytime heartburn (p<0.025), and night time heartburn (p<0.012) at both Weeks 4 and 8, with significant differences by the end of the first week of the study.

14.2 Long-term Maintenance of Healing of Erosive or Ulcerative GERD

The long-term maintenance of healing in patients with erosive or ulcerative GERD previously healed with gastric anti-secretory therapy was assessed in two U.S., multicenter, randomized, double-blind, placebo-controlled studies of identical design of 52 weeks duration. The two studies randomized 209 and 285 patients, respectively, to receive either 10 mg or 20 mg of ACIPHEX QD or placebo. As demonstrated in the tables below, ACIPHEX was significantly superior to placebo in both studies with respect to the maintenance of healing of GERD and the proportions of patients remaining free of heartburn symptoms at 52 weeks:

TABLE 10 PERCENT OF PATIENTS IN ENDOSCOPIC REMISSION
 | ACIPHEX 10 mg | ACIPHEX 20 mg | Placebo
Study 1 | N=66 | N=67 | N=70
Week 4 | 83%* | 96%* | 44%
Week 13 | 79%* | 93%* | 39%
Week 26 | 77%* | 93%* | 31%
Week 39 | 76%* | 91%* | 30%
Week 52 | 73%* | 90%* | 29%
Study 2 | N=93 | N=93 | N=99
Week 4 | 89%* | 94%* | 40%
Week 13 | 86%* | 91%* | 33%
Week 26 | 85%* | 89%* | 30%
Week 39 | 84%* | 88%* | 29%
Week 52 | 77%* | 86%* | 29%
Combined Studies | N=159 | N=160 | N=169
Week 4 | 87%* | 94%* | 42%
Week 13 | 83%* | 92%* | 36%
Week 26 | 82%* | 91%* | 31%
Week 39 | 81%* | 89%* | 30%
Week 52 | 75%* | 87%* | 29%

*(p<0.001 versus placebo)

TABLE 11 PERCENT OF PATIENTS WITHOUT RELAPSE IN HEARTBURN FREQUENCY AND DAYTIME AND NIGHTTIME HEARTBURN SEVERITY AT WEEK 52
 | ACIPHEX 10 mg | ACIPHEX 20 mg | Placebo
Heartburn Frequency
Study 1 | 46/55 (84%)* | 48/52 (92%)* | 17/45 (38%)
Study 2 | 50/72 (69%)* | 57/72 (79%)* | 22/79 (28%)
Daytime Heartburn Severity
Study 1 | 61/64 (95%)* | 60/62 (97%)* | 42/61 (69%)
Study 2 | 73/84 (87%)^+ | 82/87 (94%)* | 67/90 (74%)
Nighttime Heartburn Severity
Study 1 | 57/61 (93%)* | 60/61 (98%)* | 37/56 (66%)
Study 2 | 67/80 (84%) | 79/87 (91%)^+ | 64/87 (74%)

*p<0.001 versus placebo
^+0.001<p<0.05 versus placebo

14.3 Treatment of Symptomatic GERD

Two U.S., multicenter, double-blind, placebo controlled studies were conducted in 316 patients with daytime and nighttime heartburn. Patients reported 5 or more periods of moderate to very severe heartburn during the placebo treatment phase the week prior to randomization. Patients were confirmed by endoscopy to have no esophageal erosions.

The percentage of heartburn free daytime and/or nighttime periods was greater with ACIPHEX 20 mg compared to placebo over the 4 weeks of study in Study RAB-USA-2 (47% vs. 23%) and Study RAB-USA-3 (52% vs. 28%). The mean decreases from baseline in average daytime and nighttime heartburn scores were significantly greater for ACIPHEX 20 mg as compared to placebo at week 4. Graphical displays depicting the daily mean daytime and nighttime scores are provided in Figures 2 to 5.

FIGURE 2: MEAN DAYTIME HEARTBURN SCORES RAB-USA-2

FIGURE 3: MEAN NIGHTTIME HEARTBURN SCORES RAB-USA-2

FIGURE 4: MEAN DAYTIME HEARTBURN SCORES RAB-USA-3

FIGURE 5: MEAN NIGHTTIME HEARTBURN SCORES RAB-USA-3

In addition, the combined analysis of these two studies showed ACIPHEX 20mg significantly improved other GERD-associated symptoms (regurgitation, belching and early satiety) by week 4 compared with placebo (all p values < 0.005).

ACIPHEX 20 mg also significantly reduced daily antacid consumption versus placebo over 4 weeks (p<0.001).

14.4 Healing of Duodenal Ulcers

In a U.S., randomized, double-blind, multicenter study assessing the effectiveness of 20 mg and 40 mg of ACIPHEX QD versus placebo for healing endoscopically defined duodenal ulcers, 100 patients were treated for up to four weeks. ACIPHEX was significantly superior to placebo in producing healing of duodenal ulcers. The percentages of patients with endoscopic healing are presented below:

TABLE 12 HEALING OF DUODENAL ULCERS PERCENTAGE OF PATIENTS HEALED
Week | ACIPHEX 20 mg QD N=34 | ACIPHEX 40 mg QD N=33 | Placebo N=33
2 | 44% | 42% | 21%
4 | 79%* | 91%* | 39%

*p<0.001 versus placebo

At Weeks 2 and 4, significantly more patients in the ACIPHEX 20 and 40 mg groups reported complete resolution of ulcer pain frequency (p<0.018), daytime pain severity (p<0.023), and nighttime pain severity (p<0.035) compared with placebo patients. The only exception was the ACIPHEX 40 mg group versus placebo at Week 2 for duodenal ulcer pain frequency (p=0.094). Significant differences in resolution of daytime and nighttime pain were noted in both ACIPHEX groups relative to placebo by the end of the first week of the study. Significant reductions in daily antacid use were also noted in both ACIPHEX groups compared to placebo at Weeks 2 and 4 (p<0.001).

An international randomized, double-blind, active-controlled trial was conducted in 205 patients comparing 20 mg ACIPHEX QD with 20 mg omeprazole QD. The study was designed to provide at least 80% power to exclude a difference of at least 10% between ACIPHEX and omeprazole, assuming four-week healing response rates of 93% for both groups. In patients with endoscopically defined duodenal ulcers treated for up to four weeks, ACIPHEX was comparable to omeprazole in producing healing of duodenal ulcers. The percentages of patients with endoscopic healing at two and four weeks are presented below:

TABLE 13 HEALING OF DUODENAL ULCERS PERCENTAGE OF PATIENTS HEALED
Week | ACIPHEX 20 mg QD N=102 | Omeprazole 20 mg QD N=103 | 95% Confidence Interval for the Treatment Difference (ACIPHEX - Omeprazole)
2 | 69% | 61% | (-6%, 22%)
4 | 98% | 93% | (-3%, 15%)

ACIPHEX and omeprazole were comparable in providing complete resolution of symptoms.

14.5 Helicobacter pylori Eradication in Patients with Peptic Ulcer Disease or Symptomatic Non-Ulcer Disease

The U.S. multicenter study was a double blind, parallel group comparison of rabeprazole, amoxicillin, and clarithromycin for 3, 7, or 10 days vs. omeprazole, amoxicillin and clarithromycin for 10 days. Therapy consisted of rabeprazole 20 mg twice daily, amoxicillin 1000 mg twice daily, and clarithromycin 500 mg twice daily (RAC) or omeprazole 20 mg twice daily, amoxicillin 1000 mg twice daily, and clarithromycin 500 mg twice daily (OAC). Patients with H. pylori infection were stratified in a 1:1 ratio for those with peptic ulcer disease (active or a history of ulcer in the past five years) [PUD] and those who were symptomatic but without peptic ulcer disease [NPUD], as determined by upper gastrointestinal endoscopy. The overall H. pylori eradication rates, defined as negative ^13C-UBT for H. pylori > 6 weeks from the end of the treatment are shown in the following table. The eradication rates in the 7-day and 10-day RAC regimens were found to be similar to 10-day OAC regimen using either the Intent-to-Treat (ITT) or Per-Protocol (PP) populations. Eradication rates in the RAC 3-day regimen were inferior to the other regimens.

TABLE 14 HELICOBACTER PYLORI ERADICATION AT ≥ 6 WEEKS AFTER THE END OF TREATMENT
 | Treatment Group Percent (%) of Patients Cured (Number of Patients) |  | Difference (RAC - OAC) [95% Confidence Interval]
 | 7-day RAC* | 10-day OAC
Per Protocola | 84.3% (N=166) | 81.6% (N=179) | 2.8 [- 5.2, 10.7]
Intent-to-Treatb | 77.3% (N=194) | 73.3% (N=206) | 4.0 [- 4.4, 12.5]
 | 10-day RAC* | 10-day OAC
Per Protocola | 86.0% (N=171) | 81.6% (N=179) | 4.4 [- 3.3, 12.1]
Intent-to-Treatb | 78.1% (N=196) | 73.3% (N=206) | 4.8 [- 3.6, 13.2]
 | 3-day RAC | 10-day OAC
Per Protocola | 29.9% (N=167) | 81.6% (N=179) | -51.6 [- 60.6, -42.6]
Intent-to-Treatb | 27.3% (N=187) | 73.3% (N=206) | -46.0 [- 54.8, -37.2]

a Patients were included in the analysis if they had H. pylori infection documented at baseline, defined as a positive ^13C-UBT plus rapid urease test or culture and were not protocol violators. Patients who dropped out of the study due to an adverse event related to the study drug were included in the evaluable analysis as failures of therapy.
b Patients were included in the analysis if they had documented H. pylori infection at baseline as defined above and took at least one dose of study medication. All dropouts were included as failures of therapy.
* The 95% confidence intervals for the difference in eradication rates for 7-day RAC minus 10-day RAC are (-9.3, 6.0) in the PP population and (-9.0, 7.5) in the ITT population.

14.6 Pathological Hypersecretory Conditions, Including Zollinger-Ellison Syndrome

Twelve patients with idiopathic gastric hypersecretion or Zollinger-Ellison syndrome have been treated successfully with ACIPHEX at doses from 20 to 120 mg for up to 12 months. ACIPHEX produced satisfactory inhibition of gastric acid secretion in all patients and complete resolution of signs and symptoms of acid-peptic disease where present. ACIPHEX also prevented recurrence of gastric hypersecretion and manifestations of acid-peptic disease in all patients. The high doses of ACIPHEX used to treat this small cohort of patients with gastric hypersecretion were well tolerated.

15 REFERENCES

1. National Committee for Clinical Laboratory Standards. Methods for Dilution Antimicrobial Susceptibility Tests for Bacteria That Grow Aerobically—Fifth Edition. Approved Standard NCCLS Document M7-A5, Vol. 20, No. 2, NCCLS, Wayne, PA, January 2000.

16 HOW SUPPLIED/STORAGE AND HANDLING

ACIPHEX 20 mg is supplied as delayed-release light yellow enteric-coated tablets. The name and strength, in mg, (ACIPHEX 20) is imprinted on one side.

Bottles of 30 | NDC 54868-4185-0
Bottles of 60 | NDC 54868-4185-2
Bottles of 90 | NDC 54868-4185-1

Store at 25°C (77°F); excursions permitted to 15-30°C (59-86°F). [see USP Controlled Room Temperature] Protect from moisture.

17 PATIENT COUNSELING INFORMATION

Enter section text here

17.1 How to Take ACIPHEX

Patients should be cautioned that ACIPHEX delayed-release tablets should be swallowed whole. The tablets should not be chewed, crushed, or split. ACIPHEX can be taken with or without food.

17.2 FDA-approved patient labeling

PATIENT INFORMATION

ACIPHEX (a-se-feks)

(rabeprazole sodium)

Delayed-Release Tablets

Read the Patient Information that comes with ACIPHEX before you start taking it and each time you get a refill. There may be new information. This leaflet does not take the place of talking to your healthcare provider about your medical condition or treatment.

What is ACIPHEX?

ACIPHEX is a medicine called a proton pump inhibitor or an "acid pump inhibitor". This means it reduces the amount of acid that is made by your stomach. ACIPHEX is used in adults:

- for the short-term (4 to 8 weeks) treatment in the healing and symptom relief of damaging (erosive) Gastroesophageal Reflux Disease (GERD).
- to maintain healing of damage (erosions) and relief of heartburn symptoms with GERD. ACIPHEX has not been studied for treatment lasting longer than 12 months (1 year).
- for the treatment of daytime and nighttime heartburn and other symptoms that happen with GERD.
- for short-term treatment (up to 4 weeks) in the healing and relief of stomach-area (duodenal) ulcers. The duodenal area is the area where food passes when it leaves the stomach. The main symptom of a duodenal ulcer is a steady pain in the stomach area.
- with certain antibiotic medicines for the treatment of an infection caused by bacteria called H. pylori. Sometimes H. pylori bacteria can cause duodenal ulcers. The infection needs to be treated to prevent the ulcers from coming back.
- for the long-term treatment of conditions where your stomach makes too much acid. This includes a condition called Zollinger-Ellison syndrome.

ACIPHEX is used in adolescents 12 years of age and above:

- For the short-term (up to 8 weeks) treatment of GERD.
- The safety and effectiveness of ACIPHEX has not been established for children under the age of 12.

Who should not take ACIPHEX?

Do not take ACIPHEX if you:

- are allergic to any of the ingredients in ACIPHEX. See the end of this leaflet for a complete list of ingredients in ACIPHEX.
- are allergic to any other Proton Pump Inhibitor (PPI) medicine.

What should I tell my doctor before I take ACIPHEX?

Tell your doctor about all of your medical conditions, including if you:

- have any liver problems
- have any allergies
- are pregnant or planning to become pregnant. It is not known if ACIPHEX can harm your unborn baby.
- are breastfeeding. It is not known if ACIPHEX passes into your breast milk or if it can harm your baby. You should choose to breastfeed or take ACIPHEX, but not both. Talk to your doctor about other ways to feed your baby while taking ACIPHEX.

Tell your doctor about all the medicines you take, including prescription and non-prescription medicines, vitamins and herbal supplements. ACIPHEX and certain medicines can affect each other. This can cause serious side effects. Know the medicines that you take. Keep a list of them with you and show it to your doctor when you get a new medicine. Be sure to tell your doctor if you are taking:

- atazanavir (Reyataz)
- cyclosporine (Sandimmune, Neoral)
- digoxin (Lanoxin)
- ketoconazole (Nizoral)
- warfarin (Coumadin)
- antibiotics

How should I take ACIPHEX?

- Take ACIPHEX exactly as prescribed. Your doctor will prescribe the dose that is right for you and your medical condition. Do not change your dose or stop taking ACIPHEX unless you talk to your doctor. Take ACIPHEX for as long as it is prescribed even if you feel better.
- ACIPHEX is usually taken once a day. Your doctor will tell you the time of day to take ACIPHEX, based on your medical condition.
- ACIPHEX can be taken with or without food. Your healthcare provider will tell you whether to take this medicine with or without food based on your medical condition.
- Swallow each ACIPHEX tablet whole with water. Do not chew, crush, or split ACIPHEX tablets because this will damage the tablet and the medicine will not work. Tell your doctor if you cannot swallow tablets whole. You may need a different medicine.
- If you miss a dose of ACIPHEX, take it as soon as possible. If it is almost time for your next dose, skip the missed dose and go back to your normal schedule. Do not take 2 doses at the same time.
- If you take too much ACIPHEX, call your doctor or Poison Control Center right away, or go to the emergency room.
- Your doctor may prescribe antibiotic medicines with ACIPHEX to help treat a stomach infection and heal stomach-area (duodenal) ulcers that are caused by bacteria called H. pylori. Make sure you read the patient information that comes with an antibiotic before you start taking it.

What are the possible side effects of ACIPHEX?

ACIPHEX, like other proton pump inhibitors, may cause serious allergic reactions. See the end of this leaflet for a complete list of ingredient in ACIPHEX.

The most common side effects with ACIPHEX may include:

- headache
- pain
- pharyngitis
- flatulence
- infection
- constipation

These are not all the side effects of ACIPHEX. For more information, ask your doctor or pharmacist.

Call your healthcare provider for medical advice about side effects. You may report side effects to FDA at 1-800-FDA-1088.

How should I store ACIPHEX?

- Store ACIPHEX in a dry place at room temperature, 59°F to 86°F (15°C to 30°C).

- Keep ACIPHEX and all medicines out of the reach of children.

General Information about ACIPHEX

Medicines are sometimes prescribed for conditions other than those described in patient information leaflets. Do not use ACIPHEX for any condition for which it was not prescribed by your doctor. Do not give ACIPHEX to other people, even if they have the same symptoms as you. It may harm them.

This leaflet summarizes the most important information about ACIPHEX. If you would like more information, talk to your doctor. You can also ask your doctor or pharmacist for information about ACIPHEX that is written for healthcare professionals. For full product information, visit the website at http://www.aciphex.com/ or call the toll free number 1-888-4-ACIPHEX or 1-800 JANSSEN.

What are the ingredients in ACIPHEX?

Active Ingredient: rabeprazole sodium

Inactive ingredients of the 20 mg tablet are carnauba wax, crospovidone, diacetylated monoglycerides, ethylcellulose, hydroxypropyl cellulose, hypromellose phthalate, magnesium stearate, mannitol, propylene glycol, sodium hydroxide, sodium stearyl fumarate, talc, and titanium dioxide. Iron oxide yellow is the coloring agent for the tablet coating. Iron oxide red is the ink pigment.

The following are registered trademarks of their respective manufacturers:

Reyataz (Bristol-Myers Squibb Company), Sandimmune and Neoral (Novartis Pharmaceuticals Corporation), Lanoxin (GlaxoSmithKline), Nizoral (Janssen Pharmaceutica Products, LP), and Coumadin (Bristol-Myers Squibb Company).

What is GERD?

Your stomach needs acid to help your body digest food. Stomach acid is made by tiny acid pumps in the cells that line your stomach. If your body makes too much acid or cannot protect itself against a normal amount of acid, medical problems such as GERD can happen.

GERD happens when acid in your stomach backs up into the tube (esophagus) that connects your mouth to your stomach. Stomach acid can damage (erode) the lining of your esophagus. Some symptoms of GERD are heartburn, sour taste in the back of your throat and burping.

For prescription only

Revised June 2008

ACIPHEX is a registered trademark of Eisai Co., Ltd., Tokyo, Japan.

Manufactured and Marketed by Eisai Inc., Woodcliff Lake, NJ 06766
Marketed by PRICARA, Unit of Ortho-McNeil-Janssen Pharmaceuticals, Inc., Raritan, NJ 08869

Relabeling and Repackaging by:
Physicians Total Care, Inc.
Tulsa, OK 74146

PRINCIPAL DISPLAY PANEL

ACIPHEX 20 mg